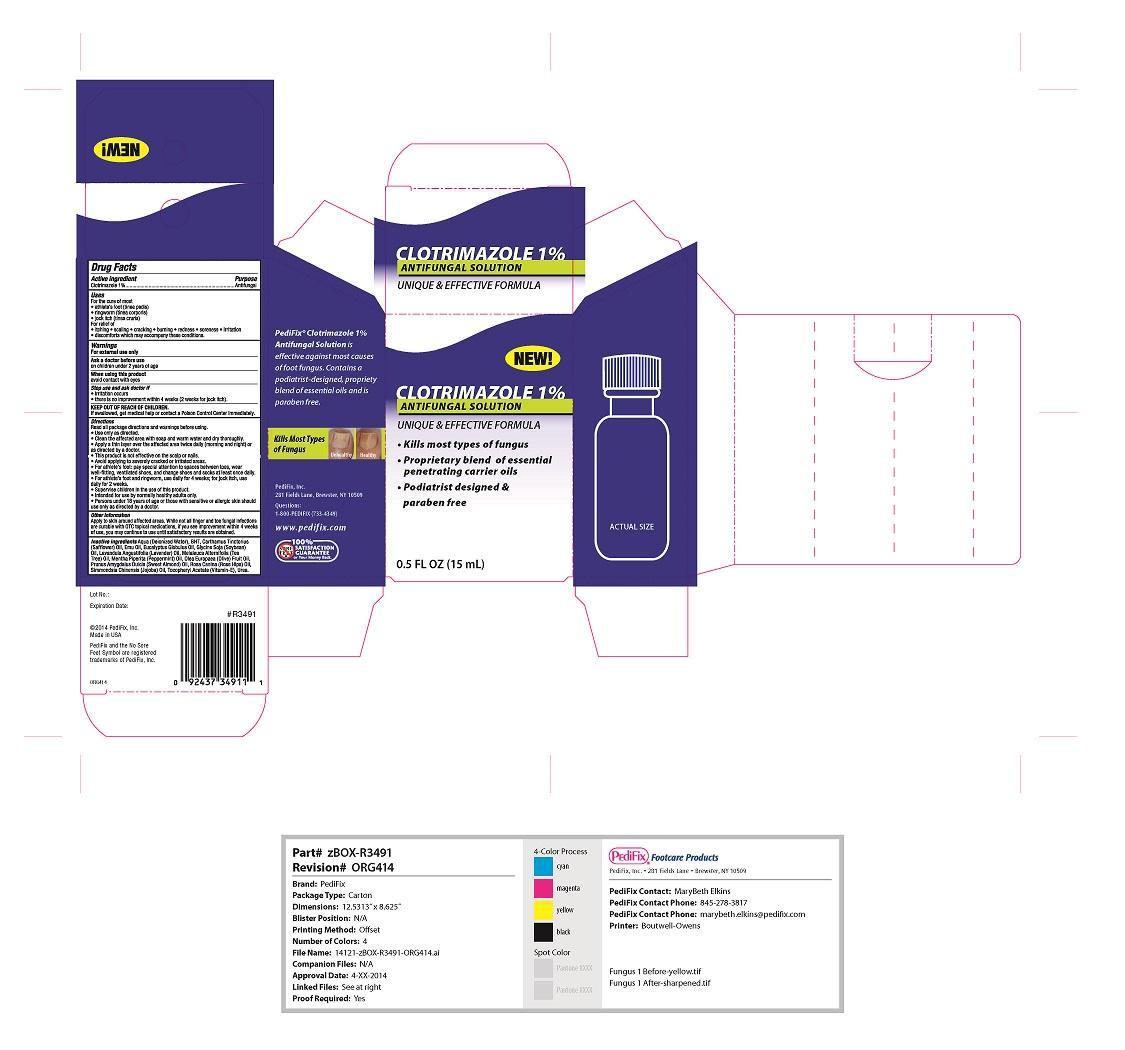 DRUG LABEL: Clotrimazole
NDC: 68927-3491 | Form: LIQUID
Manufacturer: Pedifix
Category: otc | Type: HUMAN OTC DRUG LABEL
Date: 20140507

ACTIVE INGREDIENTS: CLOTRIMAZOLE 10 mg/1 mL
INACTIVE INGREDIENTS: WATER; CARTHAMUS TINCTORIUS FLOWER OIL; EMU OIL; EUCALYPTUS GLOBULUS WHOLE; SOYBEAN OIL; LAVENDER OIL; TEA TREE OIL; PEPPERMINT OIL; OLEA EUROPAEA FRUIT VOLATILE OIL; ALMOND OIL; ROSA CANINA FLOWER OIL; JOJOBA OIL; UREA; BUTYLATED HYDROXYTOLUENE; .ALPHA.-TOCOPHEROL

Clotrimazole 1%

Warnings

For external use only
Ask a doctor before use on children under 2 years of age
When using this product avoid contact with eyes
Stop use and ask doctor if irritation occurs, there is no improvement within 4 weeks (2 weeks for jock itch)
If swallowed, get medical help or contact a poison control center immediately

Active ingredient

Clotrimazole 1%

Inactive ingredients

Aqua, BHT, safflower oil, emu oil, eucalyptus globlus oil, soybean oil, lavender oil, tea tree oil, peppermint oil, olive fruit oil, sweet almond oil, rose hip oil, jojoba oil, vitamin E, urea

Purpose

Anti-fungal

Keep out of reach of children

Directions

Read all package directions and warnings before using:
Use only as directed
Clean the affected area with soap and warm water and dry throughly
Apply a thin layer over the affected area twice daily (morning and night) or as directed by a doctor
This product is not effective on the scalp or nails
Avoid applying to severly cracked or irritated areas
For athlete's foot pay special attention to spaces between toes, wear well-fitting vetilated shoes and change shoes and socks at least once daily
For athlete's foot and ringworm use daily for 4 weeks; for jock itch use daily for 2 weeks
Supervise children in the use of this product
Intended foruse by normally healthy adults only
Persons under 18 years of age or thoes with sensitive or allergic skin should use only as directed by a doctor.

Other information

Apply to skin around affected areas. While not allfinger and toe fungal infections are curabel with OTC topical medications. If you see improvement whithin 4 weeks of use, you may continue to use until satisfactory results are obtained.